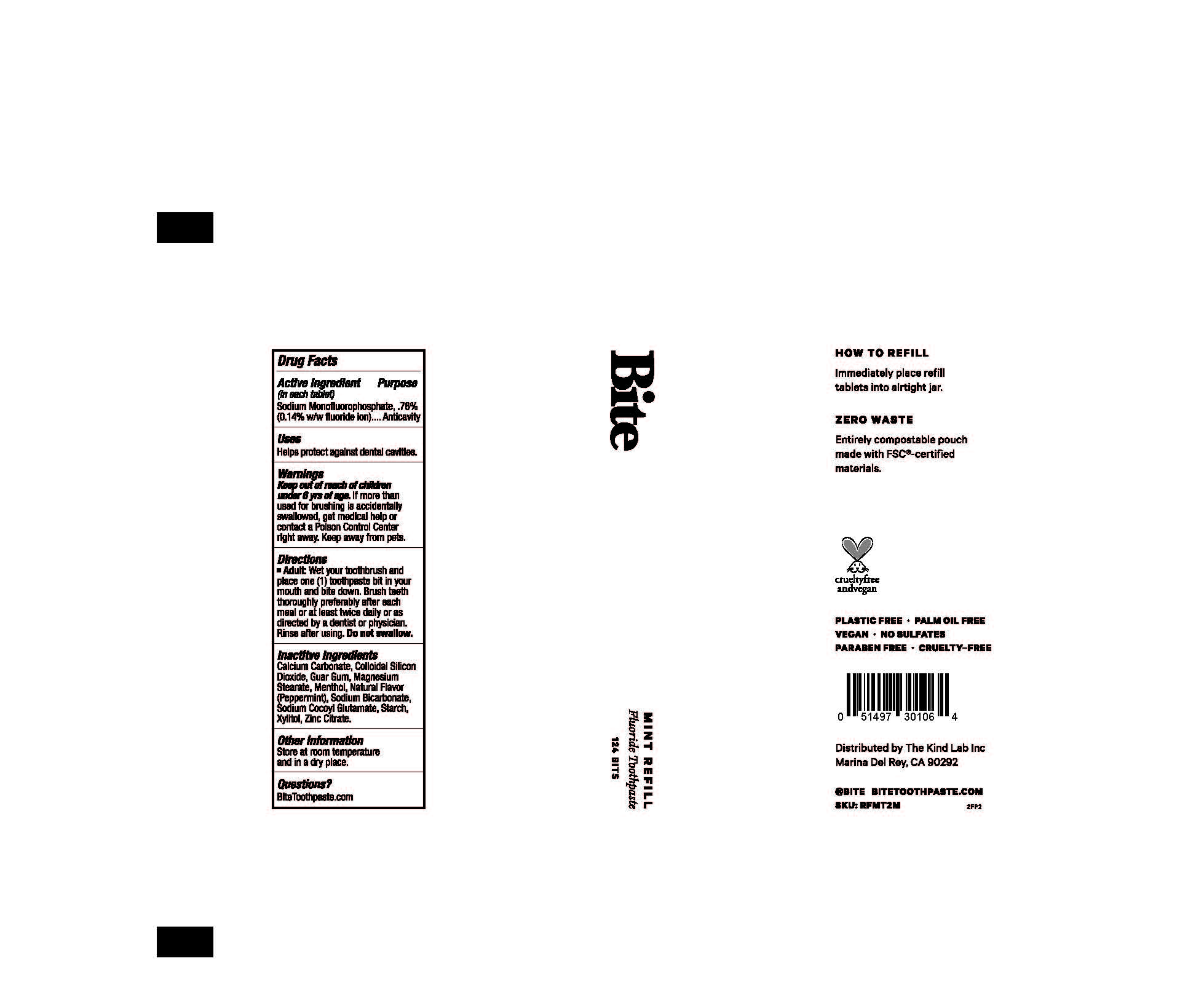 DRUG LABEL: Fluoride Bits
NDC: 82976-101 | Form: TABLET
Manufacturer: The Kind Lab, Inc.
Category: otc | Type: HUMAN OTC DRUG LABEL
Date: 20241211

ACTIVE INGREDIENTS: SODIUM MONOFLUOROPHOSPHATE 0.76 g/100 1
INACTIVE INGREDIENTS: GUAR GUM; SILICON DIOXIDE; SODIUM COCOYL GLUTAMATE; SODIUM BICARBONATE; ZINC CITRATE; STARCH, CORN; MAGNESIUM STEARATE; MENTHOL; PEPPERMINT; XYLITOL; CALCIUM CARBONATE

BITE TOOTHPASTE FLUORIDE TOOTHPASTE BITS

ACTIVE INGREDIENT

Sodium Monofluorophosphate 0.76 % (0.14 % w/w fluoride ion)

PURPOSE

Anticavity

INDICATIONS AND USAGE

Helps protect against dental cavities

WARNINGS

If more than used for brushing is accidentally swallowed, get medical help or contact Poison Control Center right away. Keep away from pets.

KEEP OUT OF REACH OF CHILDREN

Keep out of reach of childrenunder 6 years of age.

DOSAGE AND ADMINISTRATION

Adult:

Wet your toothbrush and place one (1) toothpaste bit in your mouth and bite down. Brush teeth thoroughly preferably after each meal or at least twice daily or as directed by a dentist or physician.

Rinse after using.

Do not swallow.

INACTIVE INGREDIENT

Calcium Carbonate, Colloidal Silicon Dioxide, Guar Gum, Magnesium Stearate, Menthol, Natural Flavor (Peppermint), Sodium Bicarbonate, Sodium Cocoyl Glutamate, Starch, Xylitol, Zinc Citrate.

OTHER SAFETY INFORMATION

Store at room temperature and in a dry place

QUESTIONS

BiteToothpaste.com